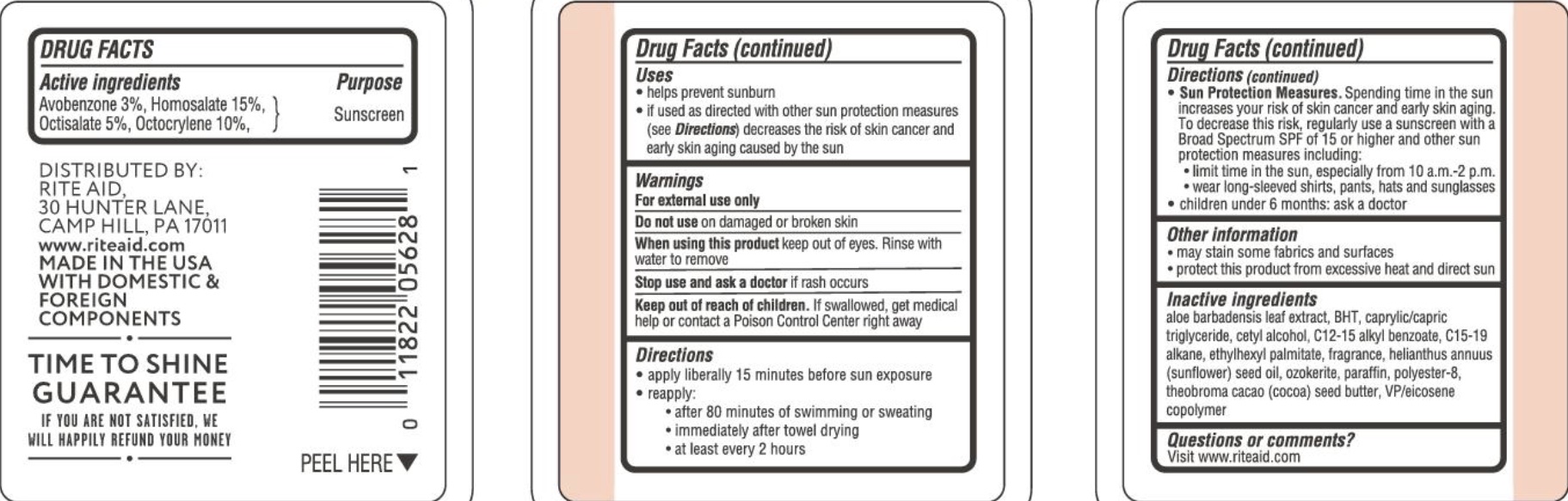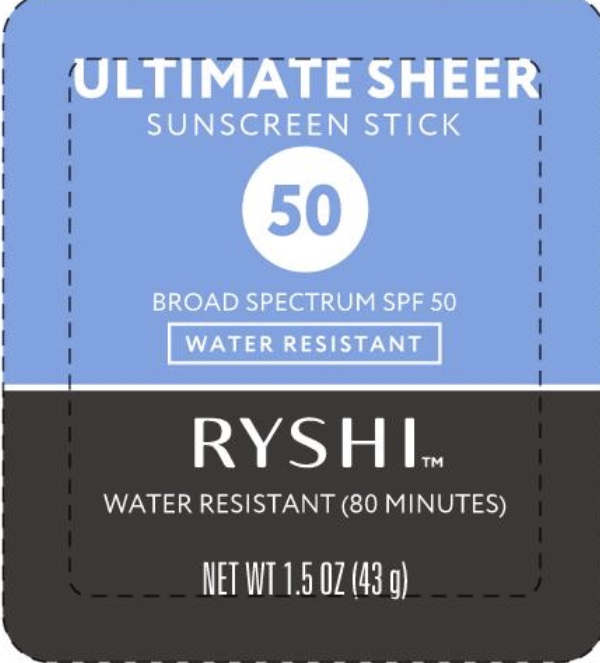 DRUG LABEL: Ryshi SPF 50 Sunscreen
NDC: 11822-3115 | Form: STICK
Manufacturer: Rite Aid
Category: otc | Type: HUMAN OTC DRUG LABEL
Date: 20241215

ACTIVE INGREDIENTS: AVOBENZONE 3 g/100 g; HOMOSALATE 15 g/100 g; OCTISALATE 5 g/100 g
INACTIVE INGREDIENTS: EICOSYL POVIDONE; CERESIN; POLYESTER-8 (1400 MW, CYANODIPHENYLPROPENOYL CAPPED); ALKYL (C12-15) BENZOATE; MEDIUM-CHAIN TRIGLYCERIDES; C15-19 ALKANE; OCTOCRYLENE 10 g/100 g; ETHYLHEXYL PALMITATE; PARAFFIN; ALOE VERA LEAF; BUTYLATED HYDROXYTOLUENE; CETYL ALCOHOL; SUNFLOWER OIL; COCOA BUTTER

PURPOSE

Sunscreen.

ACTIVE INGREDIENT

Avobenzone 3%, Homosalate 15%, Octisalate 5%, Octocrylene 10%.

INDICATIONS AND USAGE

Helps prevent sunburn. If used as directed with other sun protection measures (see Directions) decreases the risk of skin cancer and early skin aging caused by the sun.

WARNINGS

For external use only. Do not use on damaged or broken skin. When using this product keep out of eyes. Rinse with water to remove. Stop use and ask a doctor if rash occurs.

KEEP OUT OF REACH OF CHILDREN

If swallowed, get medical help or contact a Poison Control Center right away.

DOSAGE AND ADMINISTRATION

Apply liberally 15 minutes before sun exposure. Reapply after 80 minutes of swimming or sweating, immediately after towel drying, at least every 2 hours.

Sun Protection Measures. Spending time in the sun increased your risk of skin cancer and early skin aging. To decrease this risk, regularly use sunscreen with a Broad Spectrum SPF of 15 or higher and other sun protection measures including: limit time in the sun, especially from 10 am - 2 pm, wear long-sleeved shirts, pants, hats, and sunglasses. Children under 6 months: ask a doctor.

INACTIVE INGREDIENT

Aloe Barbadensis Leaf Extract, BHT, Caprylic/Capric Triglyceride, Cetyl Alcohol, C12-15 Alkyl Benzoate, C15-19 Alkane, Ethylhexyl Palmitate, Fragrance, Helianthus Annuus (Sunflower) Seed Oil, Ozokerite, Paraffin, Polyester-8, Theobroma Cacao (Cocoa) Seed Butter, VP/Eicosene Copolymer.